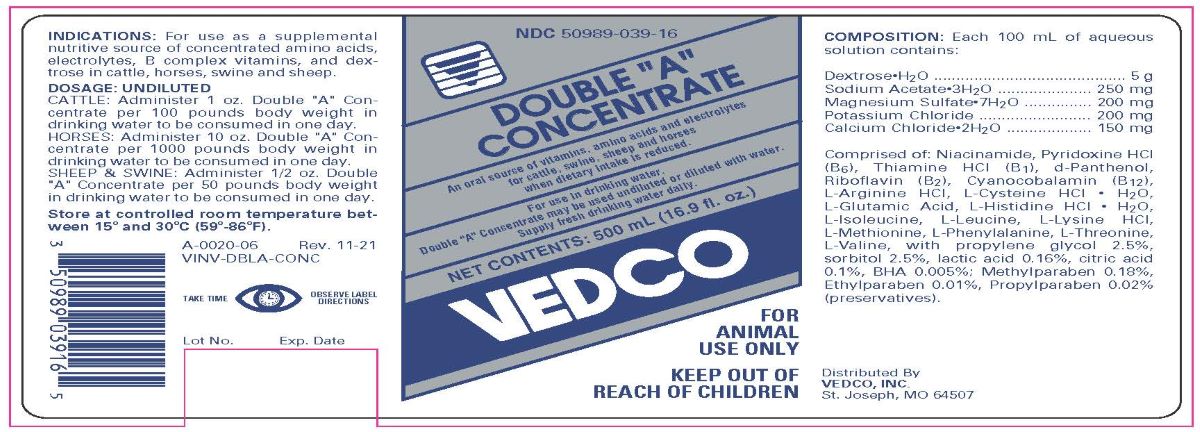 DRUG LABEL: AMINO ACID
NDC: 50989-039 | Form: CONCENTRATE
Manufacturer: Vedco, Inc.
Category: animal | Type: OTC ANIMAL DRUG LABEL
Date: 20240603

ACTIVE INGREDIENTS: CALCIUM CHLORIDE ANHYDROUS 150 mg/100 mL; DEXTROSE MONOHYDRATE 5 g/100 mL; MAGNESIUM SULFATE HEPTAHYDRATE 200 mg/100 mL; POTASSIUM CHLORIDE 200 mg/100 mL; SODIUM ACETATE ANHYDROUS 250 mg/100 mL

Double "A" Concentrate

INDICATIONS AND USAGE

FOR ANIMAL USE ONLY

KEEP OUT OF REACH OF CHILDREN

INDICATIONS

For use as a supplemental nutritive source of concentrated amino acids, electrolytes, B complex vitamins, and dextrose in cattle, horses, swine and sheep.

DOSAGE UNDILUTED

CATTLE: Administer 1 oz. Double "A" Concentrate per 100 pounds body weight in drinking water to be consumed in one day.

HORSE: Administer 10 oz. Double "A" Concentrate per 1000 pounds body weight in drinking water to be consumed in one day.

SHEEP and SWINE: Administer 1/2 oz. Double "A" Concentrate per 50 pounds body weight in drinking water to be consumed in one day.

STORAGE AND HANDLING

STORE AT CONTROLLED ROOM TEMPERATURE BETWEEN 15o and 30o C (59o-86oF)

SHAKE WELL BEFORE USING

TAKE TIME OBSERVE LABEL DIRECTIONS.

CONTENTS

Each 100 mL of aqueous solution contains:

Dextrose • H2O .......................... 5 g
Sodium Acetate • 3H2O ........ 250 mg
Magnesium Sulfate • 7H2O ... 200 mg
Potassium Chloride .............. 200 mg
Calcium Chloride • 2H2O .......150 mg

Comprised of : Niacinamide, Pyridoxine Hydrochloride (B6), Thiamine Hydrochloride (B1), d-Panthenol, Riboflavin (B2), Cyanocobalamin (B12), L-Leucine, L-Lysine Hydrochloride, L-Glutamic Acid, L-Valine, L-Phenylalanine, L-Arginine Hydrochloride, L-Isoleucine, L-Threonine, L-Histidine Hydrochloride • H2O, L-Methionine, L-Cysteine Hydrochloride • H2O, with propylne glycol 2.5%, sorbitol 2.5%, lactic acid 0.16%, citric acid 0.1%, BHA 0.005%, methylparaben 0.18%, propylparaben 0.02%, and ehtylparaben 0.01% (preservatives).